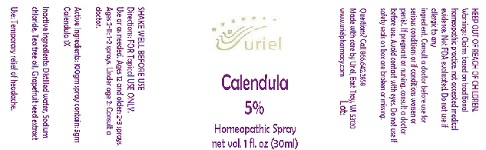 DRUG LABEL: Calendula 5% Special Order
NDC: 48951-3215 | Form: SPRAY
Manufacturer: Uriel Pharmacy Inc.
Category: homeopathic | Type: HUMAN OTC DRUG LABEL
Date: 20180508

ACTIVE INGREDIENTS: CALENDULA OFFICINALIS FLOWERING TOP 1 [hp_X]/1 mL
INACTIVE INGREDIENTS: SODIUM CHLORIDE; CITRUS PARADISI SEED; WATER; TEA TREE OIL

Calendula 5% Special Order

INDICATIONS AND USAGE

Directions: FOR Topical USE ONLY.

DOSAGE AND ADMINISTRATION

Use or as needed. Ages 12 and older: 2-3 sprays. Ages 2-11: 1-2 sprays. Under age 2: Consult a doctor.

Active Ingredients: 100gm spray contain: 5gm Calendula 1X

INACTIVE INGREDIENT

Inactive Ingredients: Distilled water, Sodium chloride, Tea tree oil, Grapefruit seed extract

PURPOSE

Use: Temporary relief of headache.

KEEP OUT OF REACH OF CHILDREN.

WARNINGS

Warnings: Claims based on traditional homeopathic practice, not accepted medical evidence. Not FDA evaluated. Do not use if allergic to any
ingredient. Consult a doctor before use for
serious conditions or if conditions worsen or
persist. If pregnant or nursing, consult a doctor before use. Avoid contact with eyes. Do not use if safety seals on box are broken or missing.

SHAKE WELL BEFORE USE

Questions? Call 866.642.2858
Made with care by Uriel, East Troy, WI 53120
www.urielpharmacy.com